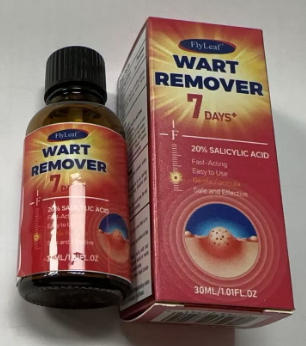 DRUG LABEL: Flyleaf WART REMOVER
NDC: 87204-166 | Form: LIQUID
Manufacturer: Guangzhou Huixue Biotechnology Co., Ltd.
Category: otc | Type: HUMAN OTC DRUG LABEL
Date: 20260206

ACTIVE INGREDIENTS: SALICYLIC ACID 6 mg/30 mL
INACTIVE INGREDIENTS: BISABOLOL; ALLANTOIN; BORNEOL; GLYCERIN; HYALURONIC ACID; WATER

ACTIVE INGREDIENT

Salicylic Acid 20%

INACTIVE INGREDIENT

Water, Borneol, Glycerin, Polyethylene Glycol, Bisabolol, Allantoin, Lonicera Japonica (Non-eysuckle) Flower Extract, Sophora Augustifolia Root Extract, Hyaluronic Acid.

PURPOSE

Wart remover

INDICATIONS AND USAGE

Uses For the removal of warts, including plantar warts, flat warts, common warts, corns, and calluses.

WARNINGS

For external use only. Flammable Keep away from fire and flame. Keep out of reach of children. Avoid contact with eyes, in case of contact, flush eyes with plenty of cool water. Do not swallow, if swallowed, seek medical attention or contact a Poison Control Center (1-800-222-1222) immediately.

KEEP OUT OF REACH OF CHILDREN

Store af room temperature Avoid excessive heat above 37°C (99°F), Skin discoloration may occur during or after use.

WHEN USING

Wash affected area. Soak the wart in warm water for 5 minutes(optional). • Use a cotton swab to apply a sufficient amount to cover each wart. Let it dry. Repeat these steps two to three times daily as needed (until the wart is removed) for up to 12 weeks.

DO NOT USE

On irritated skin or on any area that is infct . If you are allergic to any ingredient in this product. . On moles, birthmarks, warts with hair growing from them, genital warts or warts on the face or mucous membranes. .If you have diabetes or poor blood circulation. .If you are pregnant or breastfeeding unless directed by a healthcare practitioner.

STOP USE

Chest pain, rapid heart beat, faintness, or dizziness occurs sudden, unexplained weight gain occurs,your hands or feet swell.

DOSAGE AND ADMINISTRATION

Twice each day,(1ml)each time.15 days supply